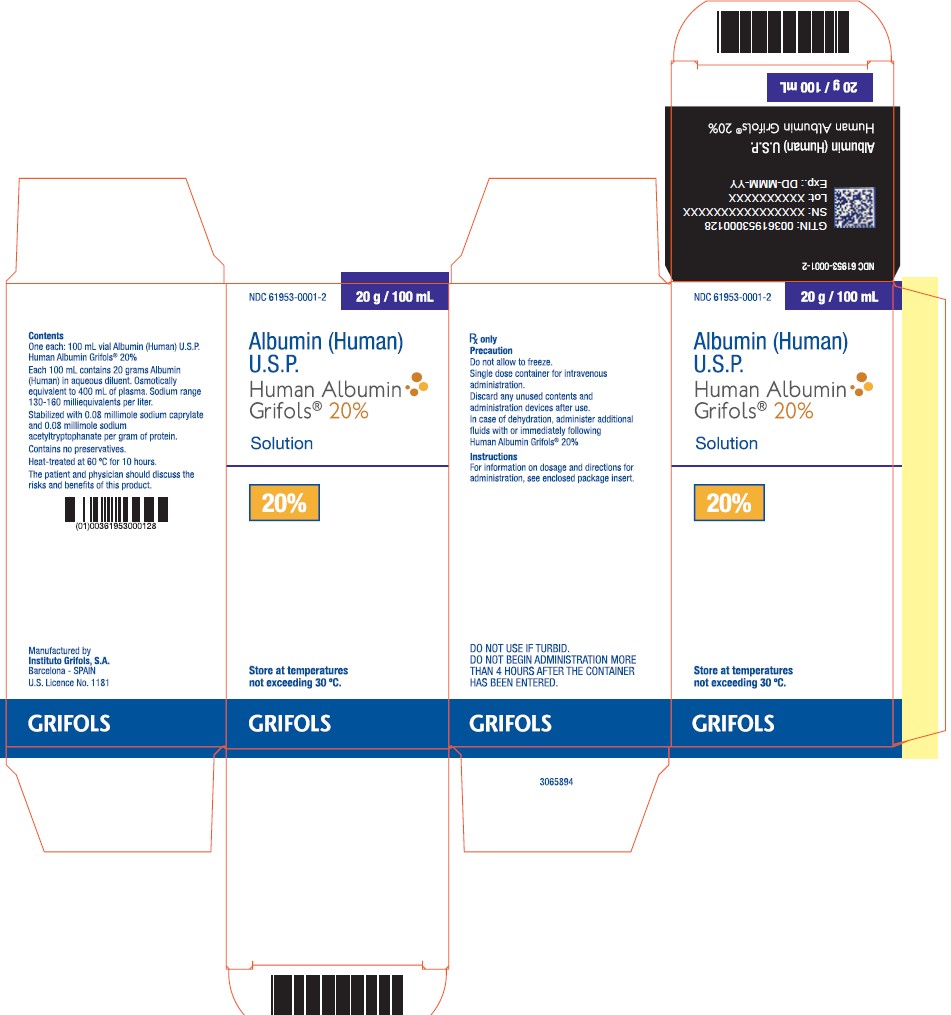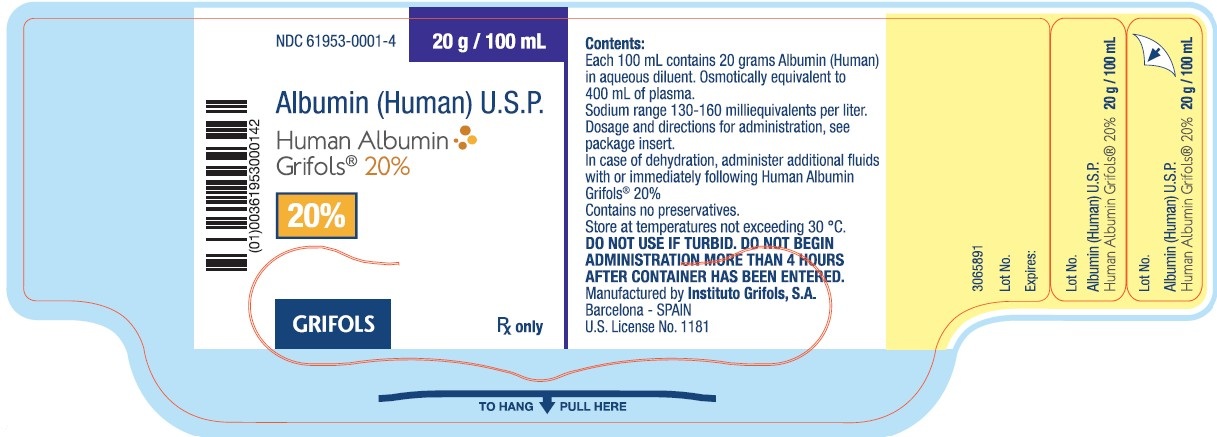 DRUG LABEL: HUMAN ALBUMIN GRIFOLS 
NDC: 61953-0001 | Form: SOLUTION
Manufacturer: GRIFOLS USA, LLC
Category: other | Type: PLASMA DERIVATIVE
Date: 20250211

ACTIVE INGREDIENTS: Albumin Human 10 g/50 mL
INACTIVE INGREDIENTS: Sodium Caprylate; Sodium Acetyltryptophanate; Water; Sodium Chloride

HIGHLIGHTS OF PRESCRIBING INFORMATION

These highlights do not include all the information needed to use Human Albumin Grifols 20% safely and effectively. See full prescribing information for Human Albumin Grifols 20%.
Human Albumin Grifols 20%
Albumin (Human) U.S.P.
20% solution
Initial U.S. Approval: 1995

1 INDICATIONS AND USAGE

Human Albumin Grifols 20% is an albumin solution indicated for:

- Hypovolemia. (1.1)
- Cardiopulmonary bypass procedures. (1.2)
- Acute nephrosis. (1.3)
- Hypoalbuminemia. (1.4)
- Ovarian hyperstimulation syndrome. (1.5)
- Neonatal hyperbilirubinemia. (1.6)
- Adult respiratory distress syndrome (ARDS). (1.7)
- Prevention of central volume depletion after paracentesis due to cirrhotic ascites. (1.8)

2 DOSAGE AND ADMINISTRATION

For Intravenous Use Only

Dosage and infusion rate should be adjusted to the patient's individual requirements.

Indication | Dose
Hypovolemia | Adults: Initial dose of 20 g (including renal dialysis). For acute liver failure: initial dose of 12 to 25 g (2.1)
Cardiopulmonary bypass procedures | Adults: Initial dose of 25 g (2.1)
Acute nephrosis | Adults: 25 g together with diuretic once a day for 7 - 10 days (2.1)
Hypoalbuminemia | Adults: 50 to 75 g For pre- and post-operative hypoproteinemia: 50 to 75 g. For burn therapy after the first 24 h: initial dose of 25 g and dose adjustment to maintain plasma protein concentration of 2.5 g per 100 mL. Third space protein loss due to infection: initial dose of 50 to 100 g (2.1)
Ovarian hyperstimulation syndrome | Adults: 50 g to 100 g over 4 hours and repeated at 4 - 12 hour intervals as necessary (2.1)
Neonatal hyperbilirubinemia | 1 g per kilogram body weight prior to or during exchange transfusion (2.1)
Adult respiratory distress syndrome (ARDS) | Adults: 25 g over 30 minutes and repeated at 8 hours for 3 days, if necessary (2.1)
Prevention of central volume depletion after paracentesis due to cirrhotic ascites | Adults: 8 g for every 1000 mL of ascitic fluid removed (2.1)

Do not dilute with sterile water for injection as this may cause hemolysis in recipients. (5.7)

3 DOSAGE FORMS AND STRENGTHS

Human Albumin Grifols 20% is a solution containing 200 g per L of total protein of which at least 95% is human albumin.

4 CONTRAINDICATIONS

- Hypersensitivity to albumin preparations or to any of the excipients.
- Severe anemia or cardiac failure with normal or increased intravascular volume. (4)

5 WARNINGS AND PRECAUTIONS

- Suspicion of allergic or anaphylactic reactions requires immediate discontinuation of the injection and implementation of appropriate medical treatment. (5.1)
- Hypervolemia may occur if the dosage and rate of infusion are not adjusted to the patient's volume status. Use with caution in conditions where hypervolemia and its consequences or hemodilution could represent a special risk to the patient. (5.2)
- When concentrated albumin is administered, care must be taken to assure adequate hydration of the patient. (5.3)
- Monitor electrolytes, coagulation and hematology parameters, and hemodynamic status when albumin is administered. (5.4, 5.5, 5.6)
- Do not dilute with sterile water for injection. (5.7)
- This product is made from human plasma and may contain infectious agents, e.g., viruses and, theoretically, the Creutzfeldt-Jakob disease agent. (5.8)

6 ADVERSE REACTIONS

The most common adverse reactions are anaphylactoid type reactions. (6)

To report SUSPECTED ADVERSE REACTIONS, contact Grifols Biologicals LLC at 1-888-GRIFOLS (1-888-474-3657) or FDA at 1-800-FDA-1088 orwww.fda.gov/medwatch.

8 USE IN SPECIFIC POPULATIONS

- Pregnancy: No human or animal data. Use only if clearly needed. (8.1)

FULL PRESCRIBING INFORMATION

1 INDICATIONS AND USAGE

1.1 Hypovolemia

For restoration and maintenance of circulating blood volume where hypovolemia is demonstrated and colloid use is appropriate. When hypovolemia is long standing and hypoalbuminemia exists accompanied by adequate hydration or edema, 20-25% albumin solutions should be used.^1,2,3

Acute liver failure is a special situation in which both hypovolemia and hypoalbuminemia can be present. Human Albumin Grifols® 20% can be used in such cases.^1

Human Albumin Grifols 20% may be of value in the treatment of shock or hypotension in renal dialysis patients.^1

1.2 Cardiopulmonary Bypass Procedures (Treatment Adjunct)

Preoperative dilution of blood using albumin and crystalloid can be used in cardiopulmonary bypass procedures. Albumin also may be used in the priming fluid.^4,5,6

1.3 Acute Nephrosis (Treatment Adjunct)

Human Albumin Grifols 20% may be used to treat peripheral edema in patients with acute nephrosis who are refractory to cyclophosphamide, corticosteroid therapy or diuretics.^1,2,7

1.4 Hypoalbuminemia

Human Albumin Grifols 20% may be indicated for subjects with hypoalbuminemia who are critically ill and/or actively bleeding. When albumin deficit is the result of excessive protein loss, the effect of Human Albumin Grifols 20% administration will be temporary unless the underlying disorder is reversed.^8,9,10

Septic patients and patients undergoing major surgery may lose more than half of their circulating plasma volume.^1,11 Treatment with Human Albumin Grifols 20% may be of value in such cases, especially when plasma colloid oncotic pressure is abnormally low.^1 In the first 24 hours after thermal injury, large volumes of crystalloids are infused to restore the depleted extracellular fluid volume. Beyond 24 hours, Human Albumin Grifols 20% can be used to maintain plasma colloid osmotic pressure.^2,12,13

Protein loss from the third space due to infection (acute peritonitis, pancreatitis, mediastinitis or extensive cellulitis) may require treatment with an infusion of albumin.^14,15

1.5 Ovarian Hyperstimulation Syndrome

Human Albumin Grifols 20% may be used as a plasma volume expander in fluid management relating to severe forms of ovarian hyperstimulation syndrome.^16,17

1.6 Neonatal Hyperbilirubinemia

Human Albumin Grifols 20% is indicated for the treatment of neonatal hyperbilirubinemia. It may be used prior to or during an exchange procedure in an attempt to bind free bilirubin and enhance its excretion.^18,19,20

1.7 Adult Respiratory Distress Syndrome (ARDS) (Treatment Adjunct)

Human Albumin Grifols 20% infusions may be indicated in conjunction with diuretics to correct fluid overload and hypoproteinemia associated with ARDS.^6,21

1.8 Prevention of Central Volume Depletion after Paracentesis due to Cirrhotic Ascites (Treatment Adjunct)

Human Albumin Grifols 20% may be used to maintain cardiovascular function following removal of large volumes of ascitic fluid after paracentesis due to cirrhotic ascites.^2,22,23,24

2 DOSAGE AND ADMINISTRATION

For Intravenous Use Only

2.1 Dosage

Adjust the concentration, dosage and infusion rate of the albumin preparation to the patient's individual requirements.

The dose required depends on the patient's body weight, severity of injury/illness and on continuing fluid and protein losses. Use adequacy of circulating blood volume, not plasma albumin levels, to determine the dose required.

Indication | Dose
Hypovolemia | Adults: Initial dose of 20 g. If hemodynamic stability is not achieved within 15 to 30 minutes, an additional dose may be given. Hemodilution may follow administration of Human Albumin Grifols 20%. Anemia resulting from hemorrhage should be corrected by administration of compatible red blood cells or compatible whole blood. For acute liver failure: initial dose of 12 to 25 g. An infusion rate of 1-2 mL per min is usually indicated. For renal dialysis, the initial dose should not exceed 20 g and patients should be carefully observed for signs of fluid overload.
Cardiopulmonary bypass procedures | Adults: Initial dose of 25 g. Additional amounts may be administered as clinically indicated.
Acute nephrosis | Adults: 25 g together with diuretic once a day for 7 - 10 days.
Hypoalbuminemia | Adults: 50 to 75 g. For pre- and post-operative hypoproteinemia: 50 to 75 g. In burns, therapy usually starts with administration of large volumes of crystalloid solution to maintain plasma volume. After 24 hours: initial dose of 25 g and dose adjustment to maintain plasma protein concentration of 2.5 g per 100 mL or a serum protein concentration of 5.2 g per 100 mL. Third space protein loss due to infection: initial dose of 50 to 100 g. An infusion rate of 1-2 mL per minute is usually indicated in the absence of shock. Treatment should always be guided by hemodynamic response.
Ovarian hyperstimulation syndrome | Adults: 50 g to 100 g over 4 hours and repeated at 4-12 hour intervals as necessary, when infusion of normal saline fails to achieve or maintain hemodynamic stability and urine output.
Neonatal hyperbilirubinemia | 1 g per kilogram body weight prior to or during exchange transfusion.
Adult respiratory distress syndrome (ARDS) | Adults: 25 g over 30 minutes and repeated at 8 hours for 3 days, if necessary.
Prevention of central volume depletion after paracentesis due to cirrhotic ascites | Adults: 8 g for every 1000 mL of ascitic fluid removed.

2.2 Administration

Intravenous use only

- Human Albumin Grifols 20% is a clear and slightly viscous solution. Visually inspect parenteral drug products for particulate matter and discoloration prior to administration, whenever solution and container permit. Do not use if the solution is turbid or if there is sediment in the bottle.
- Do not freeze.
- Warm product to room temperature before use if large volumes are administered.
- Human Albumin Grifols 20% contains no preservatives. Do not begin administration more than 4 hours after the container has been entered. Discard unused portion.
- Do not dilute with sterile water for injection. The product can be diluted in an isotonic solution (e.g., 5% Dextrose in Water or 0.9% sodium chloride) [see Warnings and Precautions (5.7)].
- Adjust the infusion rate to the individual circumstances and the indication.

3 DOSAGE FORMS AND STRENGTHS

Human Albumin Grifols 20% is a solution containing 200 g per L of total protein of which at least 95% is human albumin.

4 CONTRAINDICATIONS

- Hypersensitivity to albumin preparations or to any of the excipients.
- Severe anemia or cardiac failure with normal or increased intravascular volume.

5 WARNINGS AND PRECAUTIONS

5.1 Hypersensitivity

- Suspicion of allergic or anaphylactic reactions requires immediate discontinuation of the infusion and implementation of appropriate medical treatment.

5.2 Hypervolemia/Hemodilution

Hypervolemia may occur if the dosage and rate of infusion are not adjusted to the patient's volume status . At the first clinical signs of cardiovascular overload (headache, dyspnea, jugular venous distention, increased blood pressure), the infusion must be slowed or stopped immediately.

Use albumin with caution in conditions where hypervolemia and its consequences or hemodilution could represent a special risk to the patient. Examples of such conditions are:

- Decompensated heart failure
- Hypertension
- Esophageal varices
- Pulmonary edema
- Hemorrhagic diathesis
- Severe anemia
- Renal and post-renal anuria

5.3 Dehydration

The colloid-osmotic effect of human albumin 20% is approximately four times that of blood plasma. Therefore, when concentrated albumin is administered, care must be taken to assure adequate hydration of the patient. Patients should be monitored carefully to guard against circulatory overload and hyperhydration. Patients with marked dehydration require administration of additional fluids.

5.4 Electrolyte Imbalance

20% - 25% human albumin solutions are relatively low in electrolytes compared to 4% - 5% human albumin solutions. Monitor regularly the electrolyte status of the patient and take appropriate steps to restore or maintain the electrolyte balance when albumin is administered.

5.5 Coagulation Abnormalities

Regular monitoring of coagulation and hematology parameters is necessary if comparatively large volumes are to be replaced. Care must be taken to ensure adequate substitution of other blood constituents (coagulation factors, electrolytes, platelets and erythrocytes).

5.6 Laboratory Monitoring

Monitor regularly hemodynamic parameters during administration of Human Albumin Grifols 20%; this may include:

- Arterial blood pressure and pulse rate
- Central venous pressure
- Pulmonary artery occlusion pressure
- Urine output
- Electrolytes
- Hematocrit/hemoglobin

5.7 Application Precautions

Human Albumin Grifols 20% must not be diluted with sterile water for injection as this may cause hemolysis in recipients. The product can be diluted in an isotonic solution (e.g., 5% Dextrose in Water or 0.9% sodium chloride) [see Dosage and Administration (2.2)].

5.8 Transmissible Infectious Agents

Albumin is a derivative of human blood. Based on effective donor screening and product manufacturing processes, it carries an extremely remote risk for transmission of viral diseases. A theoretical risk for transmission of Creutzfeldt-Jakob disease (CJD) is also considered extremely remote. No cases of transmission of viral diseases or CJD have ever been identified for Human Albumin Grifols 20%.

6 ADVERSE REACTIONS

The most serious adverse reactions are anaphylactic shock, heart failure and pulmonary edema. The most common adverse reactions are anaphylactoid type reactions.

Adverse reactions to Human Albumin Grifols 20% normally resolve when the infusion rate is slowed or the infusion is stopped. In case of severe reactions, the infusion is stopped and appropriate treatment initiated.

6.1 Clinical Trials Experience

No clinical studies were done using Human Albumin Grifols 20%.

6.2 Post-marketing Experience

Because adverse reactions are reported voluntarily post-approval from a population of uncertain size, it is not always possible to reliably estimate their frequency or to establish a causal relationship to product exposure. The following adverse reactions have been identified during post-approval use of human albumin, including Human Albumin Grifols (all strengths) in decreasing order of significance:

- Anaphylactic shock
- Heart failure
- Pulmonary edema
- Hypotension
- Tachycardia
- Vomiting
- Urticaria
- Rash
- Headache
- Chills
- Fever
- Flushing
- Nausea

7 DRUG INTERACTIONS

Human Albumin Grifols 20% must not be mixed with other medicinal products.

8 USE IN SPECIFIC POPULATIONS

8.1 Pregnancy

Pregnancy Category C. Animal reproduction studies have not been conducted with Human Albumin Grifols 20%. It is also not known whether Human Albumin Grifols 20% can cause fetal harm when administered to a pregnant woman or can affect reproductive capacity. Human Albumin Grifols 20% should be given to a pregnant woman only if clearly needed.

8.2 Labor and Delivery

No human or animal data. Use only if clearly needed.

8.3 Nursing Mothers

No human or animal data. Use only if clearly needed.

8.4 Pediatric Use

No human or animal data. Use only if clearly needed.

8.5 Geriatric Use

No human or animal data. Use only if clearly needed.

11 DESCRIPTION

Human Albumin Grifols 20% is a sterile aqueous solution for single dose intravenous administration containing 20% human albumin (weight/volume). Human Albumin Grifols 20% is prepared by a cold alcohol fractionation method from pooled human plasma obtained from venous blood. The product is stabilized with 0.08 millimole sodium caprylate and 0.08 millimole sodium acetyltryptophanate per gram of protein. The colloid osmotic effect of human albumin 20% is approximately four times that of normal human plasma.

A liter of Human Albumin Grifols 20% solution contains 130 - 160 milliequivalents of sodium ion. The aluminium content of the solution is not more than 200 micrograms per liter during the shelf life of the product. The product contains no preservatives.

Human Albumin Grifols 20% is manufactured from Source Plasma collected from FDA approved plasmapheresis centers in the United States. Human Albumin Grifols 20% is heated at 60 °C for ten hours against the possibility of transmitting viruses.

12 CLINICAL PHARMACOLOGY

12.1 Mechanism of Action

Human Albumin accounts for more than half of the total protein in the plasma and represents about 10% of protein synthesis activity by the liver. Human Albumin 20% has a corresponding hyperoncotic effect.

The primary physiological function of albumin results from its contribution to plasma colloid oncotic pressure and transport function. Albumin stabilizes circulating blood volume and is a carrier of hormones, enzymes, medicinal products and toxins. Other physiological functions include antioxidant properties; free radical scavenging and capillary membrane integrity.

12.3 Pharmacokinetics

Albumin is distributed throughout the extracellular space and more than 60% of the body albumin pool is located in the extravascular fluid compartment. Albumin has a circulating life span of 15 - 20 days, with a turnover of approximately 15 g per day. The balance between synthesis and breakdown is normally achieved by feedback regulation. Elimination is predominantly intracellular and due to lysosome proteases.

In healthy subjects, less than 10% of infused albumin leaves the intravascular compartment during the first 2 hours following infusion. There is considerable individual variation in the effect of albumin on plasma volume. In some patients the plasma volume can remain elevated for several hours. In critically ill patients, however, albumin can leak out of the vascular space in substantial amounts at an unpredictable rate.

15 REFERENCES

1. Tullis, J.L., "Albumin: 1. Background and Use, 2. Guidelines for Clinical Use". JAMA 237; 355-360, 460-463, 1977.
2. Vermeulen LC et al.: A Paradigm for Consensus. Arch. Intern. Med. 1995; 155:373-379.
3. SAFE Study investigators: A comparison of albumin and saline for fluid resuscitation in the intensive care unit. N Engl J Med 2004, 350:2247-2256.
4. Sedrakyan A, Gondek K, Paltiel D, et al. Volume expansion with albumin decreases mortality after coronary artery bypass graft surgery. Chest 2003;123:1853-1857.
5. Russell JA, Navickis RJ, Wilkes MM. Albumin versus crystalloid for pump priming in cardiac surgery: meta-analysis of controlled trials. J Cardiothorac Vasc Anesth 2004;18:429-37.
6. American Thoracic Society. Evidence-based colloid use in the critically ill: American Thoracic Society consensus statement. Am J Respir Crit Care Med. 2004; 170:1247-59.
7. Fliser D, Zurbrüggen I, Mutschler E, et al. Coadministration of albumin and furosemide in patients with nephrotic syndrome. Kidney Int 1999; 55:629-34.
8. Mendez CM, McClain CJ, Marsano LS: Albumin Therapy in Clinical Practice. Nutrition in Clinical Practice 2005;20:314-320.
9. Haynes GR, Navickis RJ, Wilkes MM. Albumin administration-what is the evidence of clinical benefit? A systematic review of randomized controlled trials. Eur J Anaesthesiol. 2003 Oct;20(10):771-93.
10. Vincent JL, Navickis RJ, Wilkes MM. Morbidity in hospitalized patients receiving human albumin: a meta-analysis of randomized, controlled trials. Crit Care Med. 2004;32:2029-38.
11. Skillman JJ, Tanenbaum BJ. Current Topics in Surgical Research. Vol. 2. New York: Academic Press; 1970:523.
12. Muir IA, Barclay TL. Burns and their treatment. Chicago: Year Book Medical Publishers; 1974.
13. Pruitt BA Jr, Goodwin CW Jr. Current treatment of the extensively burned patient. Surg Annu. 1983;15:331-64.
14. Clowes GHA Jr, Vucinic M, Weidner MG: Circulatory and metabolic alterations associated with survival or death in peritonitis: clinical analysis of 25 cases. Ann Surg 1966; 166:866-85.
15. Sort P, Navasa M, Arroyo V, et al: Effect of intravenous albumin on renal impairment and mortality in patients with cirrhosis and spontaneous bacterial peritonitis. N Engl J Med 1999, 341:403-409.
16. Aboulghar M, Evers JH, Al Inany H: Intravenous albumin for preventing severe ovarian hyperstimulation syndrome: a Cochrane review. Hum.Reprod. 2002;17:3027-3032.
17. Practice Committee of the American Society for Reproductive Medicine. Ovarian hyperstimulation syndrome. Fertil.Steril. 2006;86:S178-S183.
18. Tsao YC, Yu VY: Albumin in management of neonatal hyperbilirubinaemia. Arch Dis Child 1972;47:250-256.
19. Practice parameter: management of hyperbilirubinemia in the healthy term newborn. Pediatrics 1994;94(4 pt 1):558-62.
20. Dennery PA, Seidman DS, Stevenson DK. Neonatal hyperbilirubinemia. N Eng J Med 2001;344 :581-90.
21. Martin GS et al.: A randomized, controlled trial of furosemide with or without albumin in hypoproteinemic patients with acute lung injury. Crit. Care Med. 2005; 33: 1681-1687.
22. Ginés P, Cárdenas A, Arroyo V, et al. Management of cirrhosis and ascites. N Engl J Med. 2004;350:1646-54.
23. Runyon BA. AASLD Practice Guidelines. Management of adult patients with ascites due to cirrhosis. Hepatology 2009; 49(6):2087-107.
24. Moore KP, Wong F, Ginés P, et al. The management of ascites in cirrhosis: report on the consensus conference of the International Ascites Club. Hepatology 2003; 38:258-66.

16 HOW SUPPLIED/STORAGE AND HANDLING

Human Albumin Grifols 20% is supplied in single-use, individually laser etched vials.

The following vial sizes of Human Albumin Grifols 20% are available:

NDC Number Fill Size Grams Protein
61953-0001-2 100 mL 20 g

Each vial has an integral suspension band and a label with a peel-off strip showing the product name and lot number.

Human Albumin Grifols 20% is stable for three years provided the storage temperature does not exceed 30 °C. Protect from freezing.

17 PATIENT COUNSELING INFORMATION

This product is usually given in a hospital setting.

Inform patients being treated with Human Albumin Grifols 20% about the risks and benefits of its use [see Adverse Reactions (6)].

Inform patients to immediately report the following signs and symptoms to their physician:

- Allergic or anaphylactic type reactions [see Warnings and Precautions (5.1)].
- Cardiovascular overload (e.g., headache, dyspnea and jugular venous distention) [see Warnings and Precautions (5.2)].
- Increased blood pressure, raised venous pressure and pulmonary edema [see Warnings and Precautions (5.2)].

Inform patients that Human Albumin Grifols 20% is a derivative of human plasma and may contain infectious agents that cause disease (e.g., viruses, and theoretically, the CJD agent). Inform patients that the risk that Human Albumin Grifols 20% may transmit an infectious agent has been reduced by screening plasma donors for prior exposure to certain viruses, by testing the donated plasma for certain viral agents and by the inactivation and/or removal of certain viruses during the manufacturing process [see Warnings and Precautions (5.8)].

Manufactured by:
Instituto Grifols, S.A.
Barcelona, Spain
U.S. License No. 1181
3068719

PACKAGE LABEL

Principal Display Panel – 100 mL Vial
NDC 61953-0001-4 20 g / 100 mL
Albumin (Human) U.S.P.
Human Albumin
Grifols® 20%
20%
GRIFOLS
Rx only
Contents:
Each 100 mL contains 20 grams Albumin (Human)
in aqueous diluent. Osmotically equivalent to
400 mL of plasma.
Sodium range 130-160 milliequivalents per liter.
Dosage and directions for administration, see package insert.
In case of dehydration, administer additional fluids
with or immediately following Human Albumin
Grifols® 20%
Contains no preservatives.
Store at temperatures not exceeding 30 °C.
DO NOT USE IF TURBID. DO NOT BEGIN
ADMINISTRATION MORE THAN 4 HOURS
AFTER CONTAINER HAS BEEN ENTERED.
Manufactured by Instituto Grifols, S.A.
Barcelona – SPAIN
U.S. License No. 1181
TO HANG PULL HERE
3065891
Lot No.
Expires:

PACKAGE LABEL

Principal Display Panel – 100 mL Carton
NDC 61953-0001-2 20 g / 100 mL
Albumin (Human)
U.S.P.
Human Albumin
Grifols® 20%
Solution
20%
Store at temperatures
not exceeding 30° C.
GRIFOLS
Contents
One each: 100 mL vial Albumin (Human) U.S.P.
Human Albumin Grifols® 20%
Each 100 mL contains 20 grams Albumin
(Human) in aqueous diluent. Osmotically
equivalent to 400 mL of plasma. Sodium range
130-160 milliequivalents per liter.
Stabilized with 0.08 millimole sodium caprylate
and 0.08 millimole sodium
acetyltryptophanate per gram of protein.
Contains no preservatives.
Heat-treated at 60 °C for 10 hours.
The patient and physician should discuss the
risks and benefits of this product.
Manufactured by
Instituto Grifols, S.A.
Barcelona - SPAIN
U.S. Licence No. 1181
GRIFOLS
Rx Only
Precaution
Do not allow to freeze.
Single dose container for intravenous
administration.
Discard any unused contents and
administration devices after use.
In case of dehydration, administer additional
fluids with or immediately following
Human Albumin Grifols® 20%
Instructions
For information on dosage and directions for
administration, see enclosed package insert.
DO NOT USE IF TURBID.
DO NOT BEGIN ADMINISTRATION MORE
THAN 4 HOURS AFTER THE CONTAINER
HAS BEEN ENTERED.
GRIFOLS
GTIN: 00361953000128
SN: XXXXXXXXXXXXXXXX
Lot: XXXXXXXXXX
Exp.: DD-MMM-YY
Albumin (Human) U.S.P.
Human Albumin Grifols® 20%
20 g / 100 mL
3065894